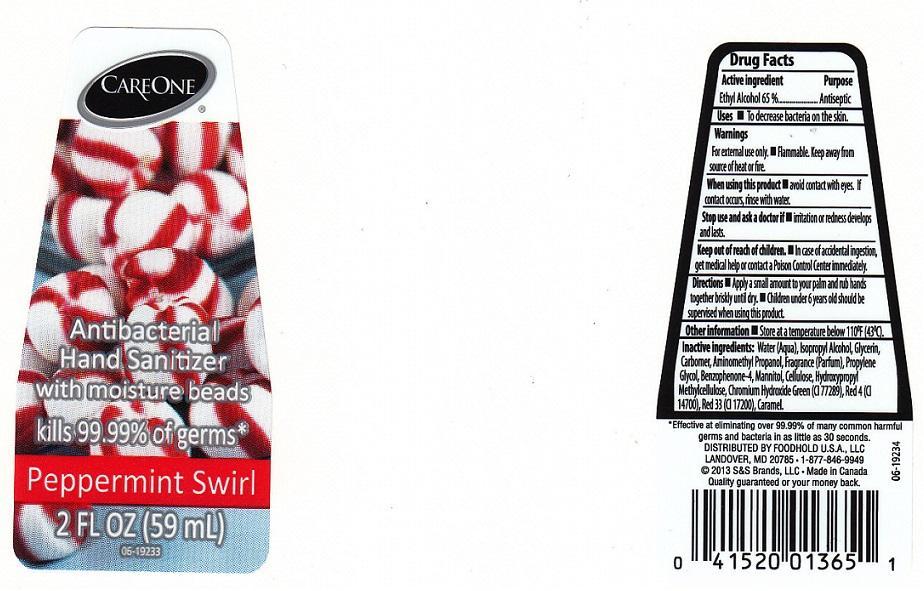 DRUG LABEL: CARE ONE
NDC: 41520-497 | Form: LIQUID
Manufacturer: AMERICAN SALES COMPANY
Category: otc | Type: HUMAN OTC DRUG LABEL
Date: 20131028

ACTIVE INGREDIENTS: ALCOHOL 650 mg/1 mL
INACTIVE INGREDIENTS: WATER; ISOPROPYL ALCOHOL; GLYCERIN; CARBOMER 934; AMINOMETHYLPROPANOL; PROPYLENE GLYCOL; SULISOBENZONE; MANNITOL; POWDERED CELLULOSE; HYPROMELLOSES; CHROMIUM HYDROXIDE GREEN; FD&C RED NO. 4; D&C RED NO. 33; CARAMEL

DRUG FACTS

ACTIVE INGREDIENT

ETHYL ALCOHOL 65%

PURPOSE

ANTISEPTIC

USES

TO DECREASE BACTERIA ON THE SKIN

WARNINGS

FOR EXTERNAL USE ONLY. FLAMMABLE. KEEP AWAY FROM SOURCE OF HEAT OR FIRE

WHEN USING THIS PRODUCT

AVOID CONTACT WITH EYES. IF CONTACT OCCURS, RINSE WITH WATER

STOP USE AND ASK A DOCTOR IF

IRRITATION OR REDNESS DEVELOPS AND LASTS

KEEP OUT OF REACH OF CHILDREN

IN CASE OF ACCIDENTAL INGESTION, GET MEDICAL HELP OR CONTACT A POISON CONTROL CENTER IMMEDIATELY

DIRECTIONS

APPLY A SMALL AMOUNT TO YOUR PALM AND RUB HANDS TOGETHER BRISKLY UNTIL DRY. CHILDREN UNDER 6 YEARS OLD SHOULD BE SUPERVISED WHEN USING THIS PRODUCT

OTHER INFORMATION

STORE AT A TEMPERATURE BELOW 110°F (43°C)

INACTIVE INGREDIENTS

WATER (AQUA), ISOPROPYL ALCOHOL, GLYCERIN, CARBOMER, AMINOMETHYL PROPANOL, FRAGRANCE (PARFUM), PROPYLENE GLYCOL, BENZOPHENONE-4, MANNITOL, CELLULOSE, HYDROXYPROPYL METHYLCELLULOSE, CHROMIUM HYDROXIDE GREEN (CI 77289), RED 4 (CI 14700), RED 33 (CI 17200), CARAMEL